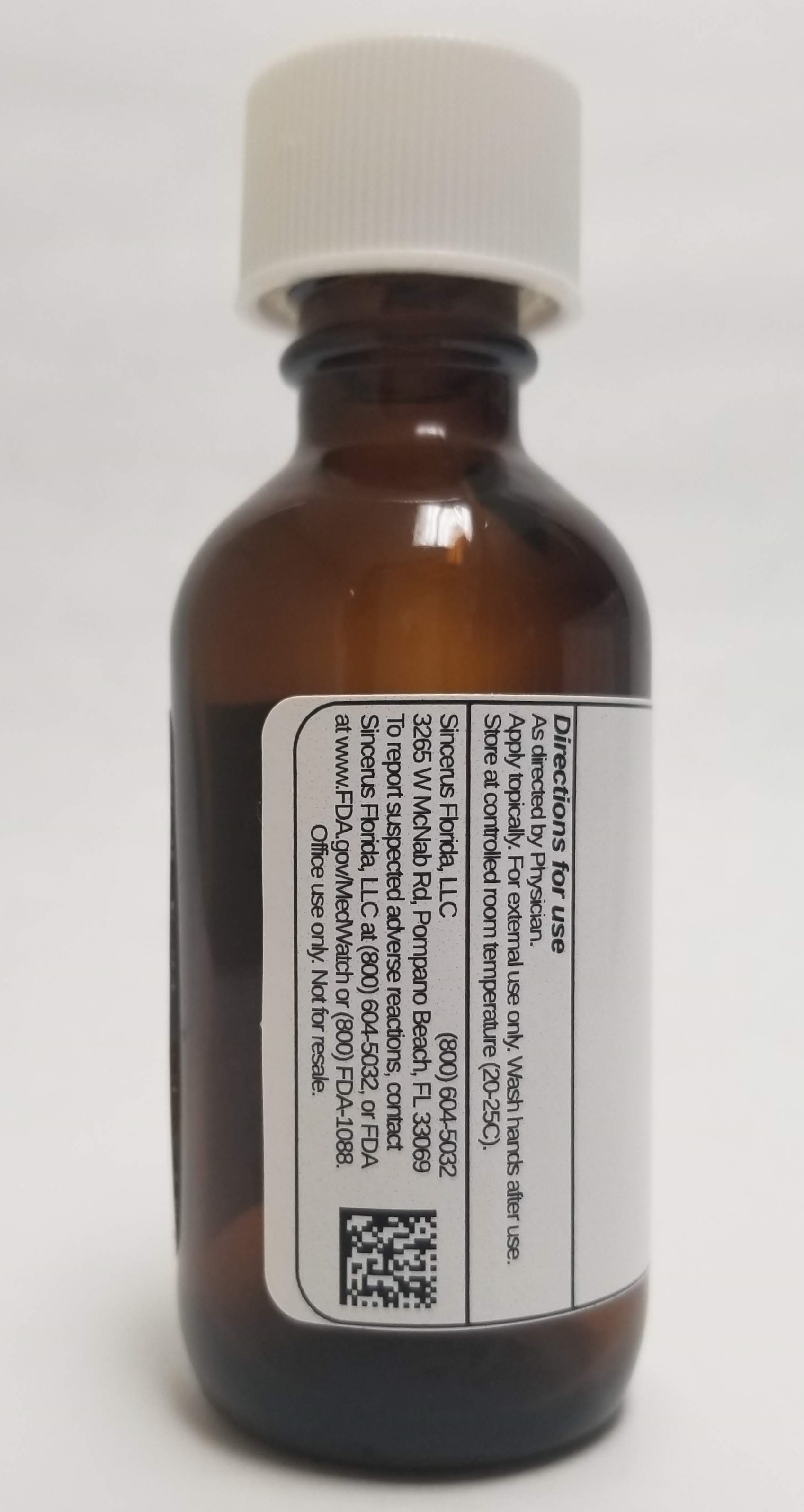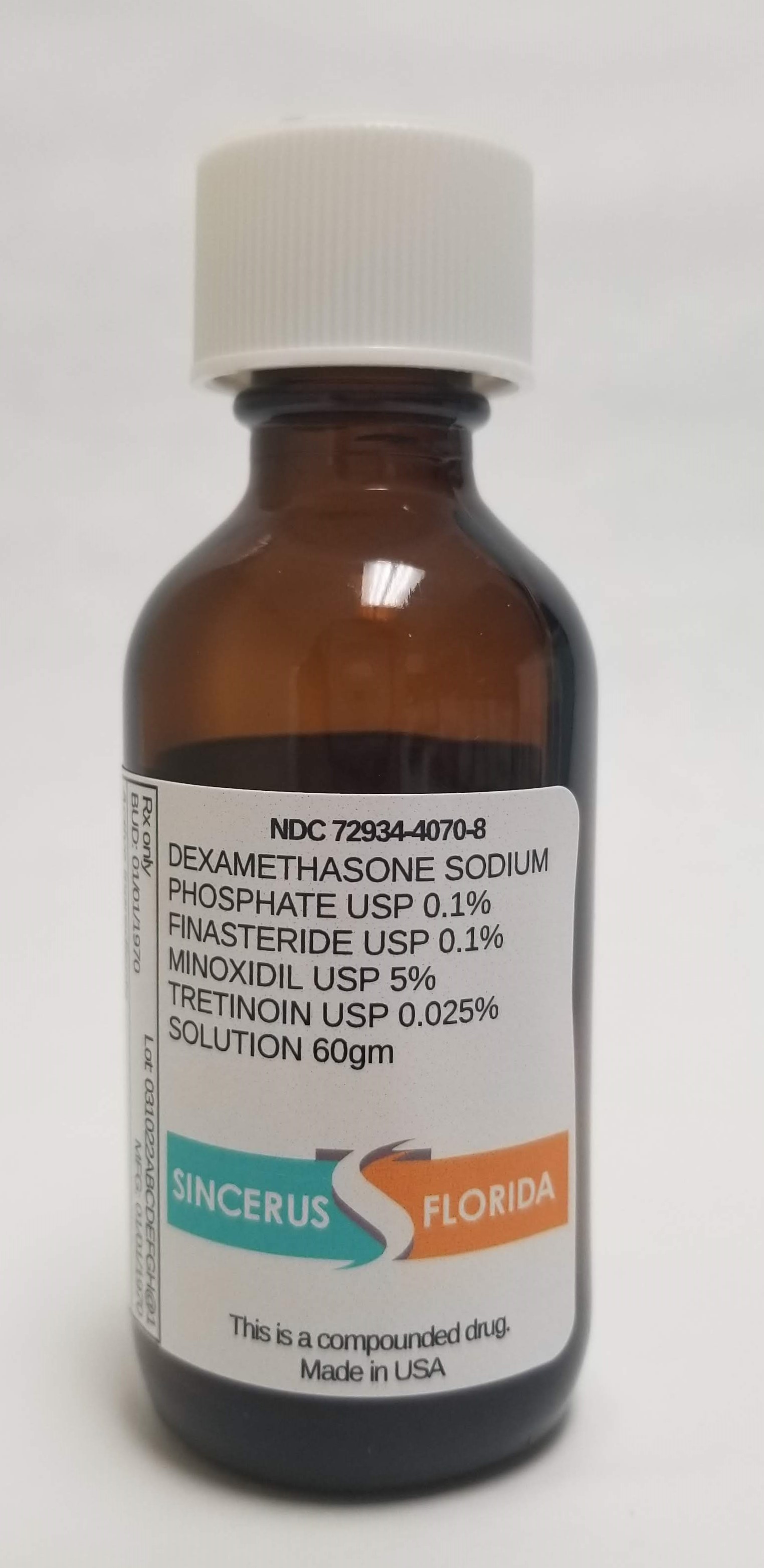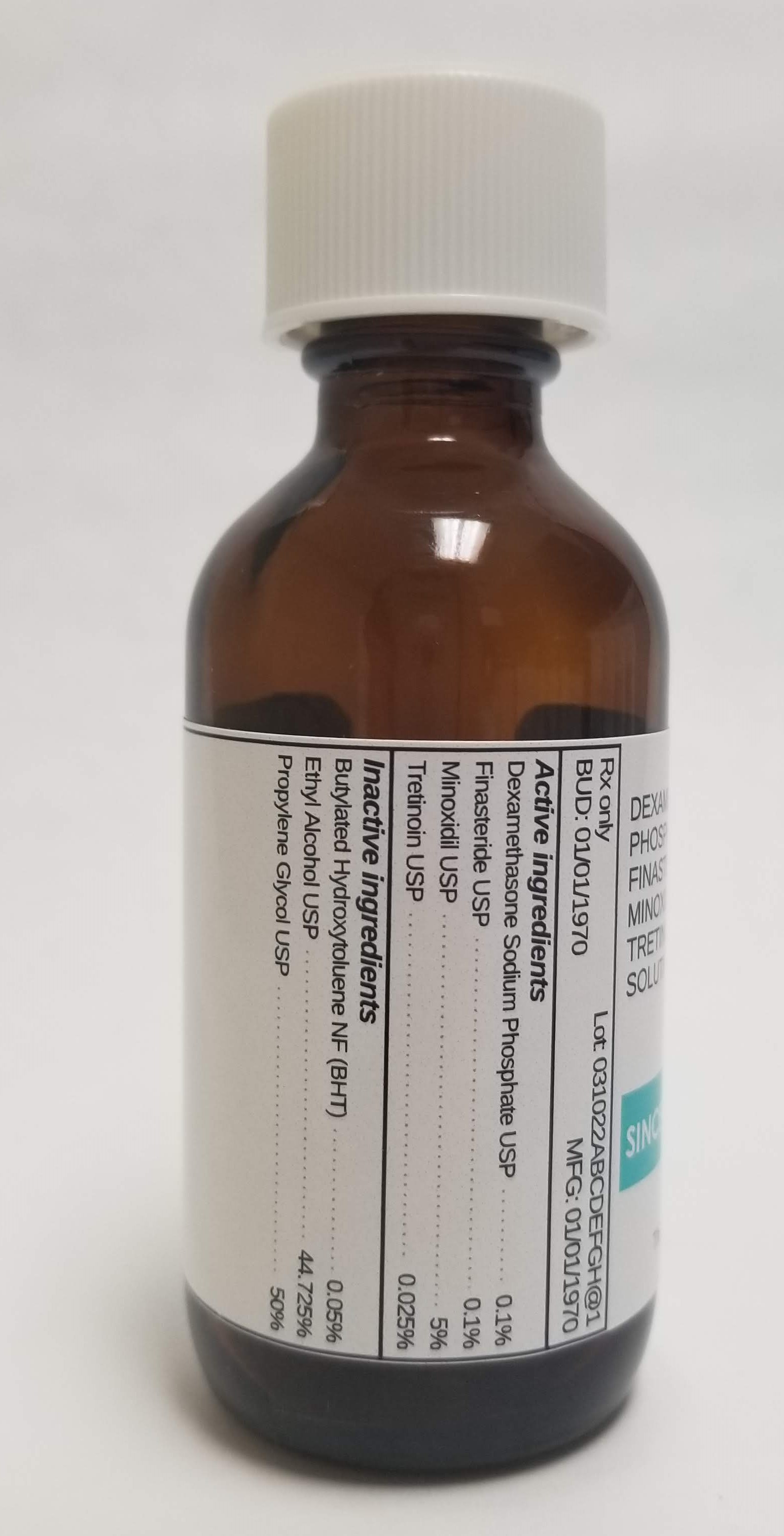 DRUG LABEL: DEXAMETHASONE SODIUM PHOSPHATE 0.1% / FINASTERIDE 0.1% / MINOXIDIL 5% / TRETINOIN 0.025%
NDC: 72934-4070 | Form: SOLUTION
Manufacturer: Sincerus Florida
Category: prescription | Type: HUMAN PRESCRIPTION DRUG LABEL
Date: 20190508

ACTIVE INGREDIENTS: DEXAMETHASONE SODIUM PHOSPHATE 0.1 g/100 g; FINASTERIDE 0.1 g/100 g; MINOXIDIL 5 g/100 g; TRETINOIN 0.025 g/100 g

DEXAMETHASONE SODIUM PHOSPHATE 0.1% / FINASTERIDE 0.1% / MINOXIDIL 5% / TRETINOIN 0.025%